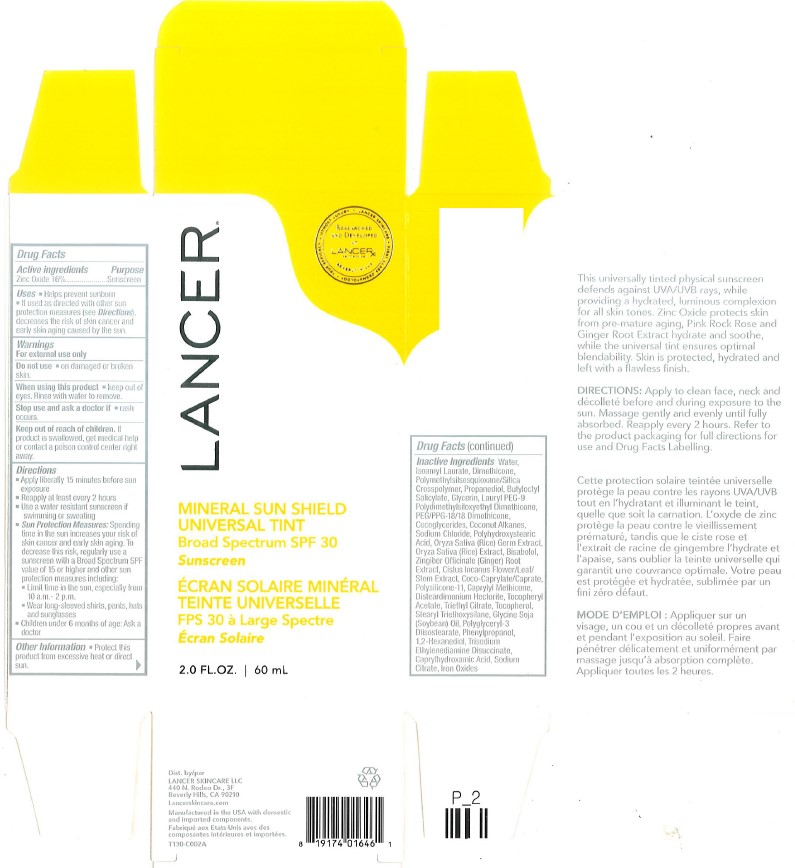 DRUG LABEL: Zinc Oxide
NDC: 67923-107 | Form: CREAM
Manufacturer: Vege Labs LLC
Category: otc | Type: HUMAN OTC DRUG LABEL
Date: 20250313

ACTIVE INGREDIENTS: ZINC OXIDE 16 mg/100 mg
INACTIVE INGREDIENTS: PROPANEDIOL; LAURYL PEG-9 POLYDIMETHYLSILOXYETHYL DIMETHICONE; POLYSILICONE-15; TRISODIUM ETHYLENEDIAMINE DISUCCINATE; GLYCINE SOJA (SOYBEAN) OIL; POLYGLYCERYL-3 DIISOSTEARATE; WATER; COCONUT ALKANES; STEARYL TRIETHOXYSILANE; POLYMETHYLSILSESQUIOXANE (11 MICRONS); BISABOLOL; CISTUS INCANUS FLOWERING TOP; .ALPHA.-TOCOPHEROL ACETATE, DL-; TRIETHYL CITRATE; PHENYLPROPANOL; CAPRYLHYDROXAMIC ACID; IRON OXIDES; COCOGLYCERIDES; ORYZA SATIVA (RICE) STARCH; ORYZA SATIVA (RICE) GERM OIL; POLYHYDROXYSTEARIC ACID (2300 MW); ZINGIBER OFFICINALE (GINGER) ROOT OIL; DISTEARDIMONIUM HECTORITE; SODIUM CHLORIDE; GLYCERIN; SODIUM CITRATE; DIMETHICONE; PEG/PPG-18/18 DIMETHICONE; COCO-CAPRYLATE/CAPRATE; CAPRYLYL METHICONE; 1,2-HEXANEDIOL; BUTYLOCTYL SALICYLATE; ISOAMYL LAURATE

Active ingredients

Zonc Oxide 16%

Purpose

Sunscreen

Uses

Helps prevent sunburn. If used as directed with other sun protection measures (see Directions), decrease the risk of sun cancer and early skin aging caused by the sun.

Warnings

For external use only

Do not use

on damages or broken skin

When using this product

Keep out of eyes. Rinse with water to remove.

Stop use and ask a doctor if

rash occurs

Keep out of reach of children

If product is swallowed, get medical help or contact a poison control center right away

Directions

Apply Liberally 15 minutes before sun exposure

Reapply at least every 2 hours

Use a water resistant sunscreen if swimming or sweating

Sun Protection Measures: Spending time in the sun increases your risk of skin cancer and early skin aging. To decrease this risk, regularly use a sunscreen with a Broad Spectrum SPF value of 15 or higher and other sun protection measures including: Limit time in the sun, especially from 10 a.m. to 2 p.m. Wear long-sleeved shirts, pants, hats and sunglasses

Children under 6 months of age: Ask a doctor

Other information

Protect this product from excessive heat or direct sun

Inactive Ingredients

Water, Isoamyl Laurate, Dimethicone, Polymethylsilsesquioxane/Silica Crosspolymer, Propanediol, Butyloctyl Salicylate, Glycerin, Lauryl PEG-9 Polydimethylsiloxyethyl Dimethicone, PEG/PPG-18/18 Dimethicone, Cocoglycerides, Coconut Alkanes, Sodium Chloride, Polyhydroxystearic Acid, Oryza Sativa (Rice) Germ Extract, Oryza Sativa (Rice) Extract, Bisabolol, Zingiber Officinale (Ginger) Root Extract, Cistus Incanus Flower/Leaf/Stem Extract, Coco-Caprylate/Caprate, Polysilicone-11, Caprylyl Methicone, Disteardimonium Hectorite, Tocopheryl Acetate, Triethyl Citrate, Tocopherol, Stearyl Triethoxysilane, Glycine Soja (Soybean) Oil, Polyglyceryl-3 Diisostearate, Phenylpropanol, 1,2-Hexanediol, Trisodium Ethylenediamine Disuccinate, Caprylhydroxamic Acid, Sodium Citrate, Iron Oxides